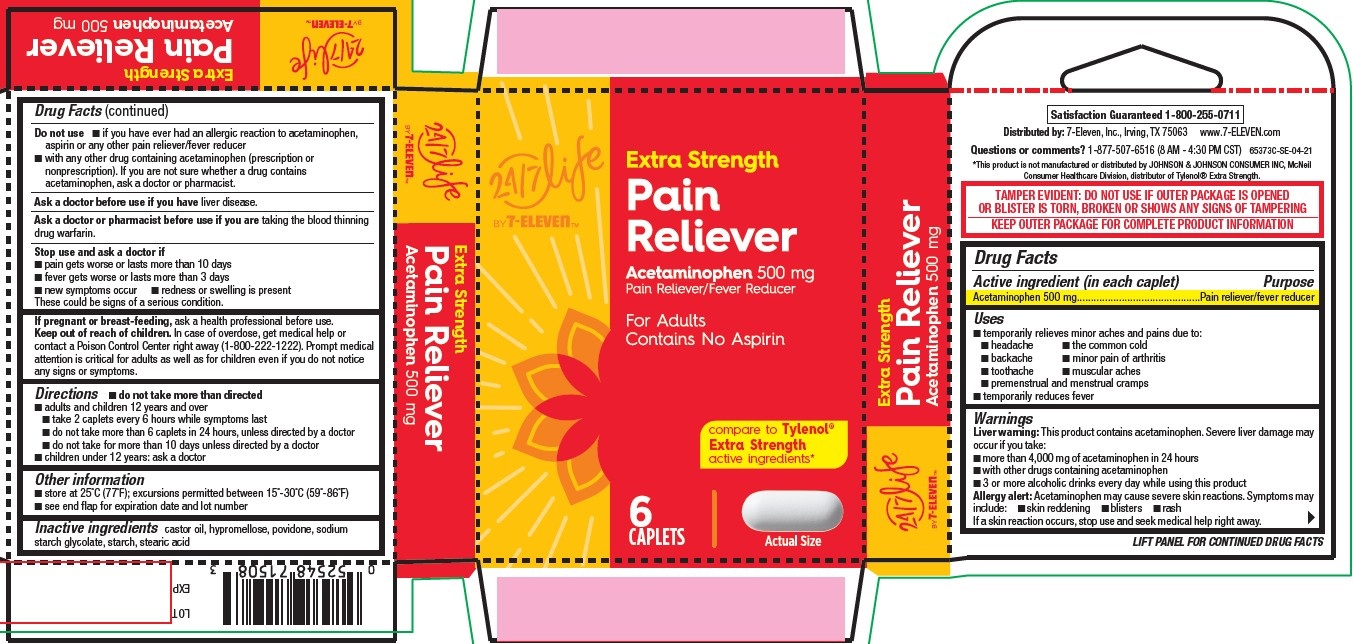 DRUG LABEL: Pain Reliever, Extra Strength, 24-7 Life by 7-Eleven
NDC: 66715-8155 | Form: TABLET
Manufacturer: Lil' Drug Store Products, Inc.
Category: otc | Type: HUMAN OTC DRUG LABEL
Date: 20251212

ACTIVE INGREDIENTS: ACETAMINOPHEN 500 mg/1 1
INACTIVE INGREDIENTS: HYPROMELLOSE, UNSPECIFIED; CASTOR OIL; POVIDONE, UNSPECIFIED; STEARIC ACID; STARCH, CORN; SODIUM STARCH GLYCOLATE TYPE A POTATO

Pain Reliever, Extra Strength, 24/7 Life by 7-ElevenTM

Drug Facts

Active ingredient

Active ingredient (in each caplet)

Acetaminophen 500 mg

Purpose

Pain reliever/fever reducer

Uses

- temporarily relieves minor aches and pains due to:
- headache
- the common cold
- backache
- minor pain of arthritis
- toothache
- muscular aches
- premenstrual and menstrual cramps
- temporarily reduces fever

Warnings

Liver warning

Liver warning: This product contains acetaminophen. Severe liver damage may occur if you take:

- more than 4,000 mg of acetaminophen in 24 hours
- with other drugs containing acetaminophen
- 3 or more alcoholic drinks every day while using this produc

Allergy alert

Allergy alert: Acetaminophen may cause severe skin reactions. Symptoms may include:

- skin reddening
- blisters
- rash

If a skin reaction occurs, stop use and seek medical help right away.

Do not use

- if you have ever had an allergic reaction to acetaminophen, aspirin or any other pain reliever/fever reducer
- with any other drug containing acetaminophen (prescription or nonprescription). If you are not sure whether a drug contains acetaminophen, ask a doctor or pharmacist.

Ask a doctor before use if you have liver disease.

Ask a doctor or pharmacist before use if you are taking the blood thinning drug warfarin.

Stop use and ask a doctor if

- pain gets worse or lasts more than 10 days
- fever gets worse or lasts more than 3 days
- new symptoms occur
- redness or swelling is present

These could be signs of a serious condition.

If pregnant or breast-feeding, ask a health professional before use.

Keep out of reach of children. In case of overdose, get medical help or contact a Poison Control Center right away (1-800-222- 222). Prompt medical attention is critical for adults as well as for children even if you do not notice any signs or symptoms.

Directions

- do not take more than directed
- adults and children 12 years and over
- take 2 caplets every 6 hours while symptoms last
- do not take more than 6 caplets in 24 hours, unless directed by a doctor
- do not take for more than 10 days unless directed by a doctor
- children under 12 years: ask a doctor

Other information

- store at 25°C (77°F); excursions permitted between 15°-30°C (59°-86°F)
- see end flap for expiration date and lot number

Inactive ingredients

castor oil, hypromellose, povidone, sodium starch glycolate, starch, stearic acid

Pain Reliever, Extra Strength, 24/7 Life by 7-ElevenTM

[ 24/7 Life by 7-ElevenTM logo]

Extra Strength

Pain

Reliever

Acetaminophen 500 mg

Pain Reliever/Fever Reducer

For Adults

Contains No Aspirin

compare to Tylenol®

Extra Strength

active ingredient*

6

CAPLETS

[caplet image]

Actual Size